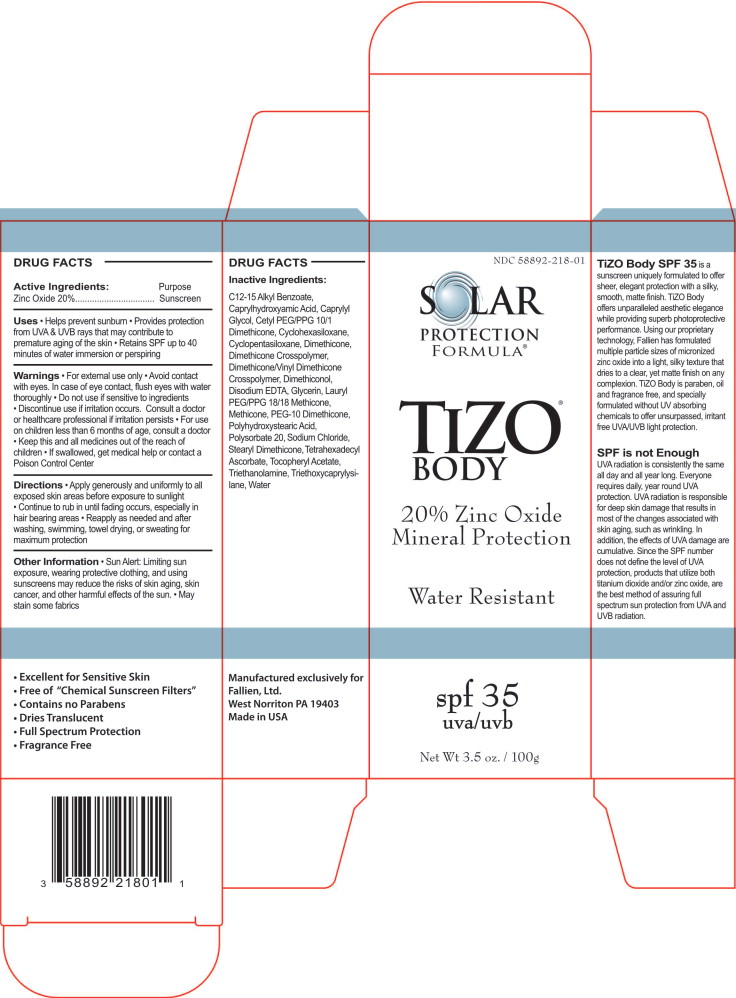 DRUG LABEL: Solar Protection Formula TiZO Body 
NDC: 58892-218 | Form: CREAM
Manufacturer: Fallien Cosmeceuticals, LTD.
Category: otc | Type: HUMAN OTC DRUG LABEL
Date: 20100902

ACTIVE INGREDIENTS: Zinc Oxide 200 mg/1 g
INACTIVE INGREDIENTS: C12-15 Alkyl Benzoate; Caprylhydroxamic Acid; Caprylyl Glycol; Cyclomethicone 6; Cyclomethicone 5; Dimethicone; Edetate Disodium; Glycerin; Hydroxystearic Acid; Polysorbate 20; Sodium Chloride; Tetrahexyldecyl Ascorbate; .Alpha.-Tocopherol Acetate, D-; Trolamine; Octyltriethoxysilane; Water

Solar Protection Formula TiZO Body Sunscreen

DRUG FACTS

Active Ingredients:

Zinc Oxide 20%

Purpose

Sunscreen

Uses

- Helps prevent sunburn
- Provides protection from UVA & UVB rays that may contribute to premature aging of the skin
- Retains SPF up to 40 minutes of water immersion or perspiring

Warnings

- For external use only
- Avoid contact with eyes. In case of eye contact, flush eyes with water thoroughly
- Do not use if sensitive to ingredients
- Discontinue use if irritation occurs. Consult a doctor or healthcare professional if irritation persists
- For use on children less than 6 months of age, consult a doctor
- Keep this and all medicines out of the reach of children
- If swallowed, get medical help or contact a Poison Control Center

Directions

- Apply generously and uniformly to all exposed skin areas before exposure to sunlight
- Continue to rub in until fading occurs, especially in hair bearing areas
- Reapply as needed and after washing, swimming, towel drying, or sweating for maximum protection

Other Information

- Sun Alert: Limiting sun exposure, wearing protective clothing, and using sunscreens may reduce the risks of skin aging, skin cancer, and other harmful effects of the sun.
- May stain some fabrics

Inactive Ingredients:

C12-15 Alkyl Benzoate, Caprylhydroxyamic Acid, Caprylyl Glycol, Cetyl PEG/PPG 10/1 Dimethicone, Cyclohexasiloxane, Cyclopentasiloxane, Dimethicone, Dimethicone Crosspolymer, Dimethicone/Vinyl Dimethicone Crosspolymer, Dimethiconol, Disodium EDTA, Glycerin, Lauryl PEG/PPG 18/18 Methicone, Methicone, PEG-10 Dimethicone, Polyhydroxystearic Acid, Polysorbate 20, Sodium Chloride, Stearyl Dimethicone, Tetrahexadecyl Ascorbate, Tocopheryl Acetate, Triethanolamine, Triethoxycaprylysilane, Water

TiZO Body SPF 35 is a sunscreen uniquely formulated to offer sheer, elegant protection with a silky, smooth, matte finish. TiZO Body offers unparalleled aesthetic elegance while providing superb photoprotective performance. Using our proprietary technology, Fallien has formulated multiple particle sizes of micronized zinc oxide into a light, silky texture that dries to a clear, yet matte finish on any complexion. TiZO Body is paraben, oil and fragrance free, and specially formulated without UV absorbing chemicals to offer unsurpassed, irritant free UVA/UVB light protection.

SPF is not Enough

UVA radiation is consistently the same all day and all year long. Everyone requires daily, year round UVA protection. UVA radiation is responsible for deep skin damage that results in most of the changes associated with skin aging, such as wrinkling. In addition, the effects of UVA damage are cumulative. Since the SPF number does not define the level of UVA protection, products that utilize both titanium dioxide and/or zinc oxide, are the best method of assuring full spectrum sun protection from UVA and UVB radiation.

- Excellent for Sensitive Skin
- Free of "Chemical Sunscreen Filters"
- Contains no Parabens
- Dries Translucent
- Full Spectrum Protection
- Fragrance Free

Manufactured exclusively for
Fallien, Ltd.
West Norriton PA 19403
Made in USA

Principal Display Panel – Carton Label

NDC 58892-218-01

SOLAR

PROTECTION

Formula®

TIZO®

BODY

20% Zinc Oxide Mineral Protection

Water Resistant

spf 35

uva/uvb

Net Wt 3.5 oz. / 100g